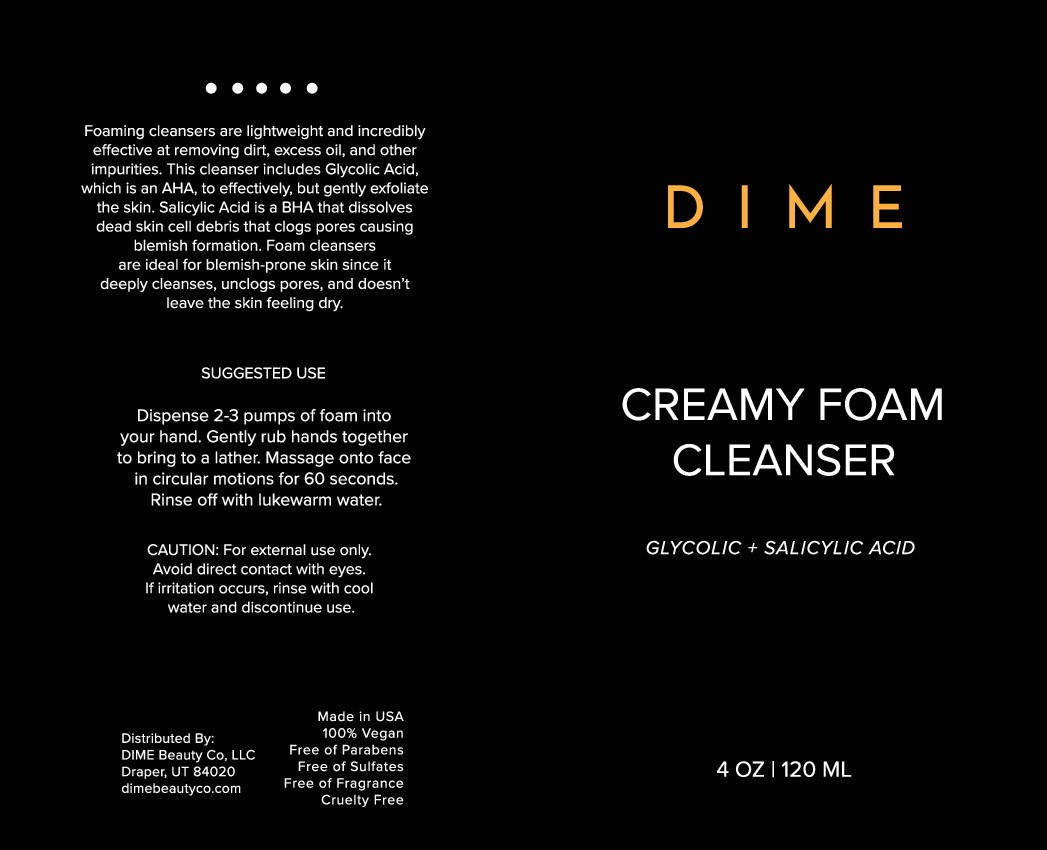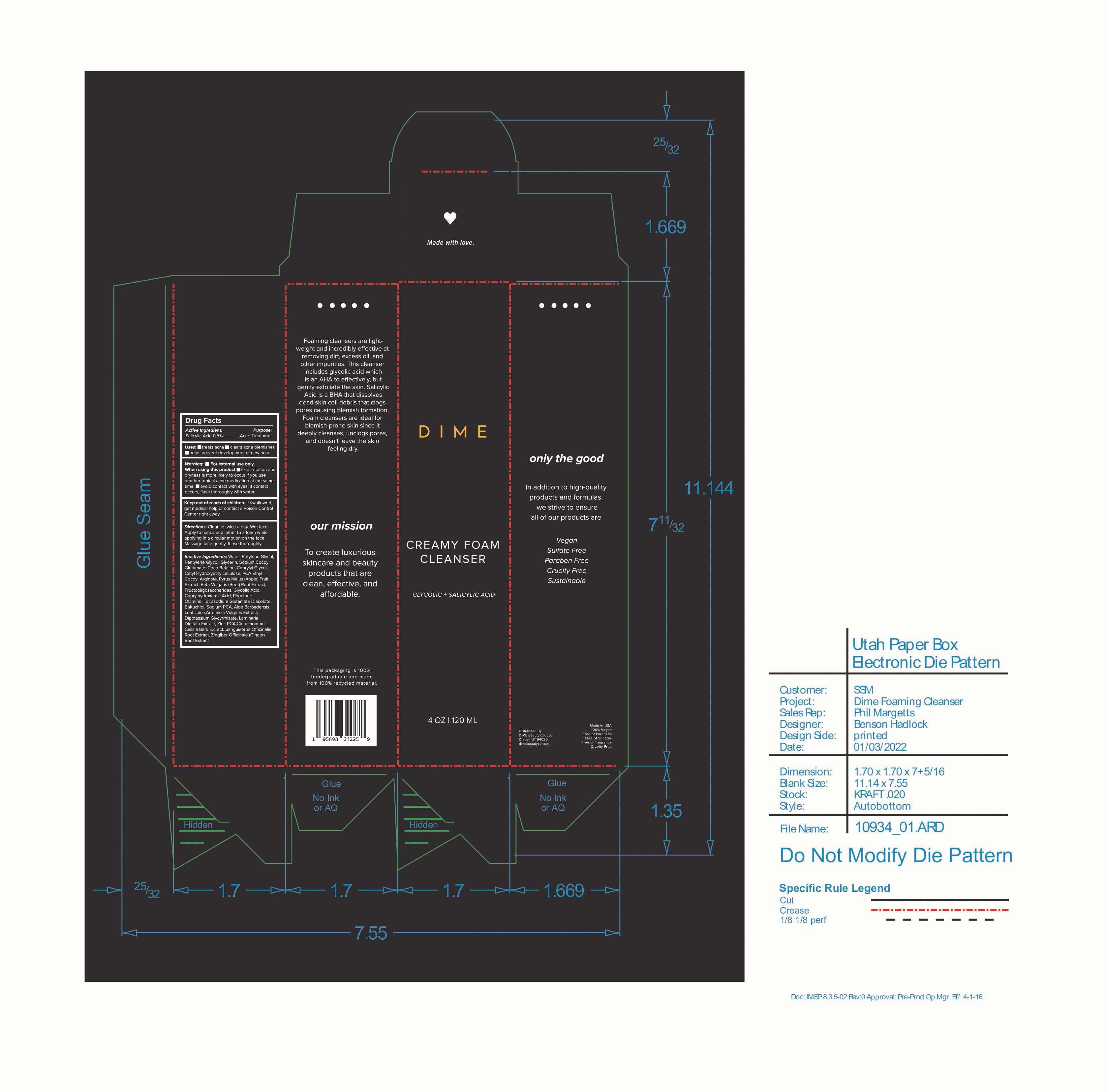 DRUG LABEL: Creamy Foam Cleanser
NDC: 82870-002 | Form: CREAM
Manufacturer: Dime Beauty Co, LLC
Category: otc | Type: HUMAN OTC DRUG LABEL
Date: 20251001

ACTIVE INGREDIENTS: SALICYLIC ACID 0.5 g/100 mL
INACTIVE INGREDIENTS: GLYCERIN; CETYL HYDROXYETHYLCELLULOSE (350000 MW); GLYCOLIC ACID; PIROCTONE OLAMINE; BEET; WATER; SODIUM COCOYL GLUTAMATE; PYRROLIDONE CARBOXYLIC ACID ETHYL COCOYL ARGINATE; CAPRYLHYDROXAMIC ACID; BUTYLENE GLYCOL; PENTYLENE GLYCOL; COCO-BETAINE; GLYCYRRHIZINATE DIPOTASSIUM; SANGUISORBA OFFICINALIS ROOT; APPLE; CAPRYLYL GLYCOL; SODIUM PYRROLIDONE CARBOXYLATE; ALOE VERA LEAF; CHINESE CINNAMON; BAKUCHIOL; TETRASODIUM GLUTAMATE DIACETATE; LAMINARIA DIGITATA; ZINC PIDOLATE

Creamy Foam Cleanser

Active Ingredient: Purpose:

Salicylic Acid 0.5% Acne Treatment

Uses:

- treats acne
- clears acne blemishes
- helps prevent development of new acne

Keep out of reach of children. If swallowed, get medical help or contact a Poison Control Center right away

When using this product

- Skin Irritation and dryness is more likely to occur if you use another topical acne medication at the same time

WARNINGS

Warning: For External Use only.

avoid contact with eyes. If contact occurs, flush thoroughly eyes with water.

Directions:

Cleanse Twice a day. Wet face. Apply to hands and lather to a foam while applying in a circular motion on the face. Massage face gently. RInse Thoroughly.

INACTIVE INGREDIENT

Inactive Ingredients: Water, Butylene Glycol, Pentylene Glycol, Glycerin, Sodium Cocoyl Glutamate, Coco Betaine, Caprylyl Glycol, Cetyl Hydroxyethylcellulose, PCA Ethyl Cocoyl Arginate, Pyrus Malus (Apple) Fruit Extract, Beta Vulgaris (Beet) Root Extract, Fructooligosaccharides, Glycolic Acid, Caprylhydroxamic Acid, Piroctone Olamine, Tetrasodium Glutamate Diacetate, Bakuchiol, Sodium PCA, Aloe Barbadensis Leaf Juice, Artemisia Vulgaris Extract, Dipotassium Glycyrrhizate, Laminaria Digitata Extract, Zinc PCA, Cinnamomum Cassia Bark Extract, Sanguisorba Officinalis Root Extract, Zingiber Officinale (Ginger) Root Extract

PACKAGE LABEL

DIME

CREAMY FOAM CLEANSER

GLYCOLIC + SALICYLIC ACID

4 oz 120mL